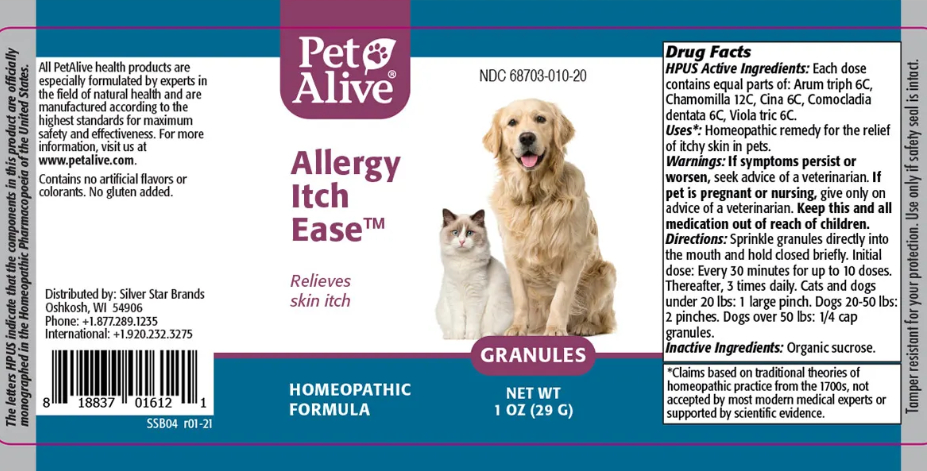 DRUG LABEL: PetAlive Allergy Itch Ease
NDC: 68703-010 | Form: GRANULE
Manufacturer: SILVER STAR BRANDS
Category: homeopathic | Type: OTC ANIMAL DRUG LABEL
Date: 20251212

ACTIVE INGREDIENTS: ARISAEMA TRIPHYLLUM ROOT 6 [hp_C]/16 mg; MATRICARIA RECUTITA 12 [hp_C]/16 mg; ARTEMISIA CINA PRE-FLOWERING TOP 6 [hp_C]/16 mg; COMOCLADIA DENTATA BARK/LEAF 6 [hp_C]/16 mg; VIOLA TRICOLOR 6 [hp_C]/16 mg
INACTIVE INGREDIENTS: SUCROSE

PetAlive Allergy Itch Ease

PURPOSE

Relieves skin itch

ACTIVE INGREDIENT

HPUS Active Ingredients: Each dose contains equal parts of:

Arum triph 6C

Chamomilla 12C

Cina 6C

Comocladia dentata 6C

Viola tric 6C

INDICATIONS AND USAGE

Uses: Homeopathic remedy for the relief of itchy skin in pets

WARNINGS

Warnings: If symptoms persist or worsen, seek advice of a veterinarian.

PREGNANCY OR BREAST FEEDING

If pet is pregnant or nursing, give only on advice of a veterinarian

KEEP OUT OF REACH OF CHILDREN

Keep this and all medication out of reach of children.

DOSAGE AND ADMINISTRATION

Directions: Sprinkle granules directly into the mouth and hold closed briefly. Initial dose: Every 30 minutes for up to 10 doses. Thereafter, 3 times daily. Cats and dogs under 20 lbs: 1 large pinch. Dogs 20-50 lbs 2 pinches. Dogs over 50 lbs: 1/4 cap granules.

Inactive Ingredients: Organic sucrose.

INFORMATION FOR OWNERS/CAREGIVERS

The letters HPUS indicate that the components in this products in this product are officially monographed in the Homeopathic Pharmacopoeia of the United States

All PetAlive health products are especially formulated by experts in the field of natural health and are manufactured according to the highest standards for maximum safety and effectiveness. For more information, visit us at www.petalive.com.

Contains no artificial flavors or artificial colors. No gluten added.

Distributed by: Silver Star Brands
Oshkosh, WI 54906
Phone: +1.877.289.1235
International: +1.920.232.3275

STORAGE AND HANDLING

Tamper resistant for your protection. Use only if safety seal is intact